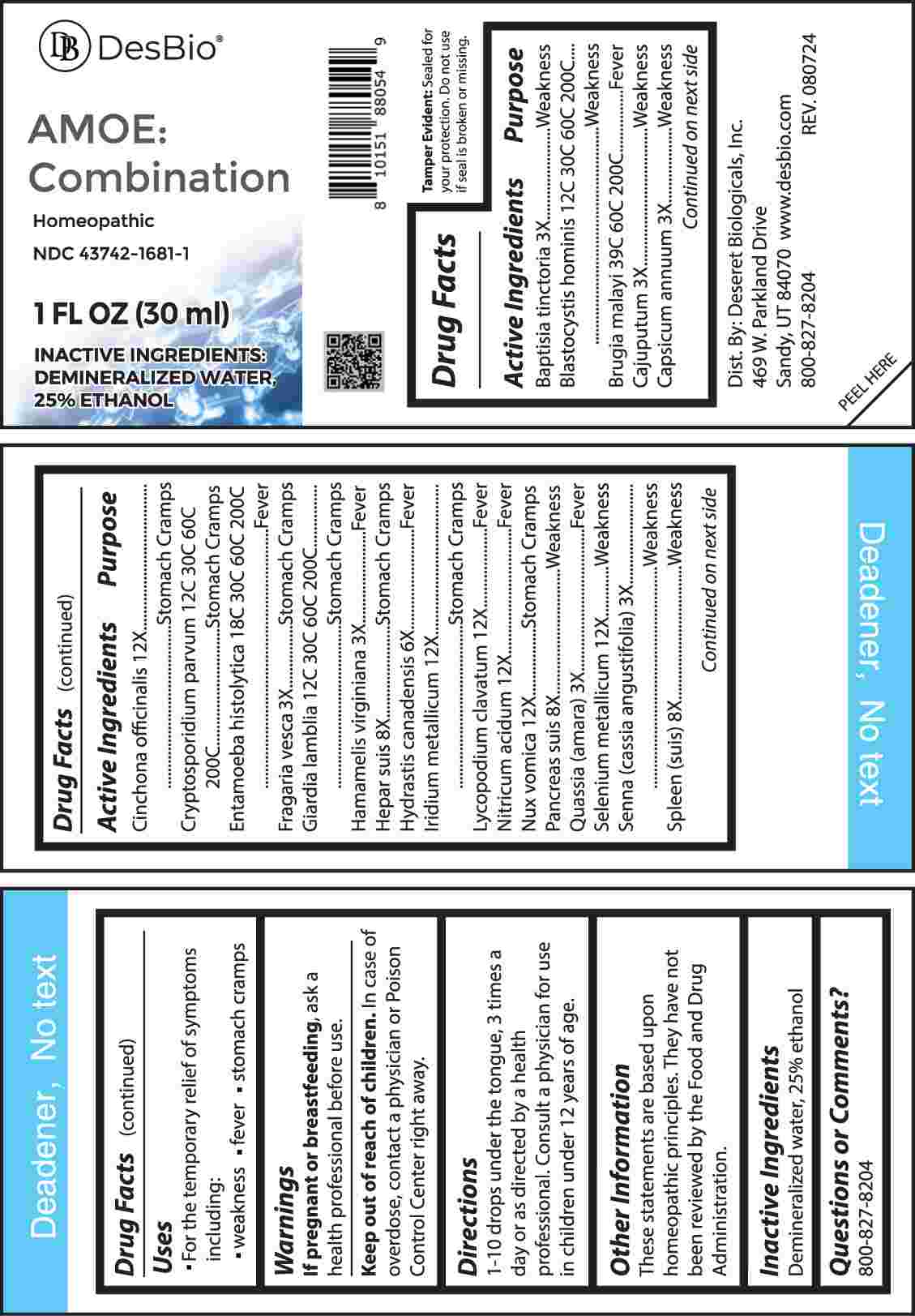 DRUG LABEL: Amoe Combination
NDC: 43742-1681 | Form: LIQUID
Manufacturer: Deseret Biologicals, Inc.
Category: homeopathic | Type: HUMAN OTC DRUG LABEL
Date: 20241022

ACTIVE INGREDIENTS: BAPTISIA TINCTORIA ROOT 3 [hp_X]/1 mL; CAJUPUT OIL 3 [hp_X]/1 mL; CAPSICUM 3 [hp_X]/1 mL; FRAGARIA VESCA FRUIT 3 [hp_X]/1 mL; HAMAMELIS VIRGINIANA ROOT BARK/STEM BARK 3 [hp_X]/1 mL; QUASSIA AMARA WOOD 3 [hp_X]/1 mL; SENNA LEAF 3 [hp_X]/1 mL; GOLDENSEAL 6 [hp_X]/1 mL; PORK LIVER 8 [hp_X]/1 mL; SUS SCROFA PANCREAS 8 [hp_X]/1 mL; SUS SCROFA SPLEEN 8 [hp_X]/1 mL; CINCHONA OFFICINALIS BARK 12 [hp_X]/1 mL; IRIDIUM 12 [hp_X]/1 mL; LYCOPODIUM CLAVATUM SPORE 12 [hp_X]/1 mL; NITRIC ACID 12 [hp_X]/1 mL; STRYCHNOS NUX-VOMICA SEED 12 [hp_X]/1 mL; SELENIUM 12 [hp_X]/1 mL; BLASTOCYSTIS HOMINIS 12 [hp_C]/1 mL; CRYPTOSPORIDIUM PARVUM 12 [hp_C]/1 mL; GIARDIA LAMBLIA 12 [hp_C]/1 mL; ENTAMOEBA HISTOLYTICA 18 [hp_C]/1 mL; BRUGIA MALAYI 39 [hp_C]/1 mL
INACTIVE INGREDIENTS: WATER; ALCOHOL

DRUG FACTS:

ACTIVE INGREDIENTS:

Baptisia Tinctoria 3X, Blastocystis Hominis 12C, 30C, 60C, 200C, Brugia Malayi 39C, 60C, 200C, Cajuputum 3X, Capsicum Annuum 3X, Cinchona Officinalis 12X, Cryptosporidium Parvum 12C, 30C, 60C, 200C, Entamoeba Histolytica 18C, 30C, 60C, 200C, Fragaria Vesca 3X, Giardia Lamblia 12C, 30C, 60C, 200C, Hamamelis Virginiana 3X, Hepar Suis 8X, Hydrastis Canadensis 6X, Iridium Metallicum 12X, Lycopodium Clavatum 12X, Nitricum Acidum 12X, Nux Vomica 12X, Pancreas Suis 8X, Quassia (Amara) 3X, Selenium Metallicum 12X, Senna (Cassia Angustifolia) 3X, Spleen (Suis) 8X.

PURPOSE:

Baptisia Tinctoria - Weakness, Blastocystis Hominis - Weakness, Brugia Malayi – Fever, Cajuputum - Weakness, Capsicum Annuum - Weakness, Cinchona Officinalis – Stomach Cramps, Cryptosporidium Parvum – Stomach Cramps, Entamoeba Histolytica - Fever, Fragaria Vesca – Stomach Cramps, Giardia Lamblia – Stomach Cramps, Hamamelis Virginiana - Fever, Hepar Suis – Stomach Cramps, Hydrastis Canadensis - Fever, Iridium Metallicum – Stomach Cramps, Lycopodium Clavatum - Fever, Nitricum Acidum - Fever, Nux Vomica – Stomach Cramps, Pancreas Suis - Weakness, Quassia (Amara) - Fever, Selenium Metallicum - Weakness, Senna (Cassia Angustifolia) - Weakness, Spleen (Suis) - Weakness.

USES:

• For the temporary relief of symptoms including:

• weakness • fever • stomach cramps

These statements are based upon homeopathic principles. They have not been reviewed by the Food and Drug Administration.

WARNINGS:

If pregnant or breast-feeding, ask a health professional before use.

Keep out of reach of children. In case of overdose, contact a physician or Poison Control Center right away.

Tamper Evident: Sealed for your protection. Do not use if seal is broken or missing.

KEEP OUT OF REACH OF CHILDREN:

In case of overdose, contact a physician or Poison Control Center right away.

DIRECTIONS:

1-10 drops under the tongue, 3 times a day or as directed by a health professional. Consult a physician for use in children under 12 years of age.

INACTIVE INGREDIENTS:

Demineralized water, 25% ethanol

QUESTIONS:

Dist. By: Deseret Biologicals, Inc.

469 W. Parkland Drive

Sandy, UT 84070 www.desbio.com

800-827-8204

PACKAGE LABEL DISPLAY:

DesBio

AMOE:

Combination

Homeopathic

NDC 43742-1681-1
1 FL OZ (30 ml)